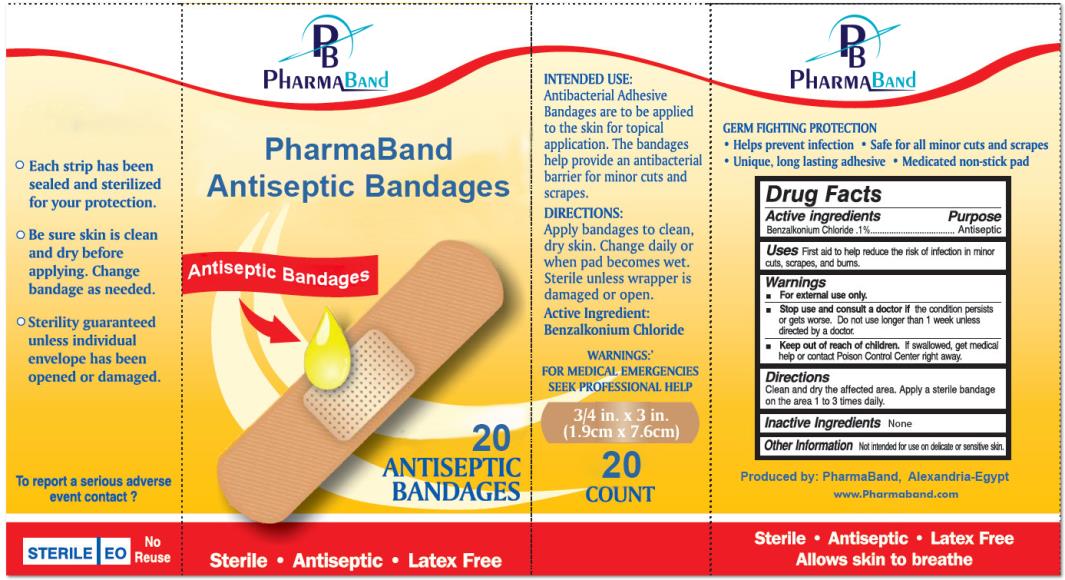 DRUG LABEL: Antiseptic Bandages
NDC: 69225-1000 | Form: DRESSING
Manufacturer: Pharmaband
Category: otc | Type: HUMAN OTC DRUG LABEL
Date: 20140922

ACTIVE INGREDIENTS: BENZALKONIUM CHLORIDE 0.042 mg/1 1

Antiseptic Bandages

Drug Facts

Active ingredients

Benzalkonium Chloride 0.1%

Purpose

Antiseptic

Uses

First aid to help reduce the risk of infection in minor cuts, scrapes, and burns

Warnings

- For external use only.

Stop use and consult a doctor

if the condition persists or gets worse. Do not use longer than 1 week unless directed by a doctor.

Keep out of reach of children.

If swallowed, get medical help or contact Poison Control Center right away.

Directions

Clean and dry the affected area. Apply a sterile bandage on the area 1 to 3 times daily.

Inactive Ingredients:

None

Other Information:

Not intended for use on delicate or sensitive skin.

PRINCIPAL DISPLAY PANEL

PharmaBand
Antiseptic Bandages
20
Antiseptic
Bandages